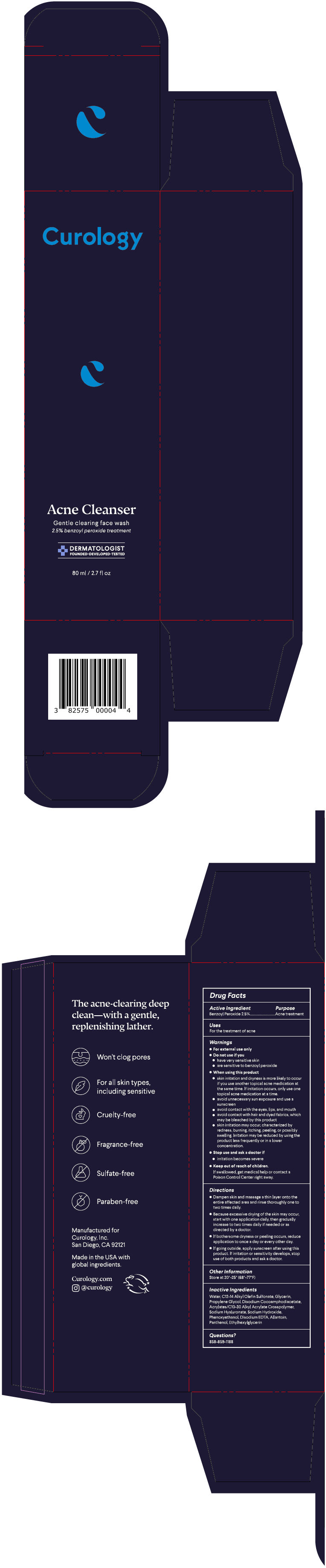 DRUG LABEL: CA22 Benzoyl Peroxide Cleansing
NDC: 82575-122 | Form: GEL
Manufacturer: Curology Inc.
Category: otc | Type: HUMAN OTC DRUG LABEL
Date: 20221208

ACTIVE INGREDIENTS: Benzoyl Peroxide 25 mg/1 mL
INACTIVE INGREDIENTS: Water; SODIUM C12-14 OLEFIN SULFONATE; Glycerin; Propylene Glycol; Disodium Cocoamphodiacetate; CARBOMER HOMOPOLYMER, UNSPECIFIED TYPE; Hyaluronate Sodium; Sodium Hydroxide; Phenoxyethanol; EDETATE DISODIUM ANHYDROUS; Allantoin; Panthenol; Ethylhexylglycerin

CA22 Benzoyl Peroxide Cleansing Gel 2.5%

Drug Facts

Active Ingredient

Benzoyl Peroxide 2.5%

Purpose

Acne treatment

Uses

For the treatment of acne

Warnings

For external use only

Do not use if you

have very sensitive skin

are sensitive to benzoyl peroxide

When using this product

skin irritation and dryness is more likely to occur if you use another topical acne medication at the same time. If irritation occurs, only use one topical acne medication at a time.

avoid unnecessary sun exposure and use a sunscreen.

avoid contact with the eyes, lips, and mouth

avoid contact with hair and dyed fabrics, which may be bleached by this product.

skin irritation may occur, characterized by redness, burning, itching, peeling, or possibly swelling. Irritation may be reduced by using the product less frequently or in a lower concentration.

Stop use and ask a doctor if

irritation becomes severe

Keep out of reach of children.

If swallowed, get medical help or contact a Poison Control Center right away.

Directions

Dampen skin and massage a thin layer onto the entire affected area and rinse thoroughly one to two times daily.

Because excessive drying of the skin may occur, start with one application daily, then gradually increase to two times daily if needed or as directed by a doctor.

If bothersome dryness or peeling occurs, reduce application to once a day or every other day.

If going outside, apply sunscreen after using this product. If irritation or sensitivity develops, stop use of both products and ask a doctor.

Other Information

Store at 20°-25° (68°-77°F)

Inactive Ingredients

Water, C12-14 Alkyl Olefin Sulfonate, Glycerin, Propylene Glycol, Disodium Cocoamphodiacetate, Acrylates/C10-30 Alkyl Acrylate Crosspolymer, Sodium Hyaluronate, Sodium Hydroxide, Phenoxyethanol, Disodium EDTA, Allantoin, Panthenol, Ethylhexylglycerin

Questions?

858-859-1188

PRINCIPAL DISPLAY PANEL - 80 ml Tube Box

Curology

Acne Cleanser

Gentle clearing face wash
2.5% benzoyl peroxide treatment

DERMATOLOGIST
FOUNDED•DEVELOPED•TESTED

80 ml / 2.7 fl oz